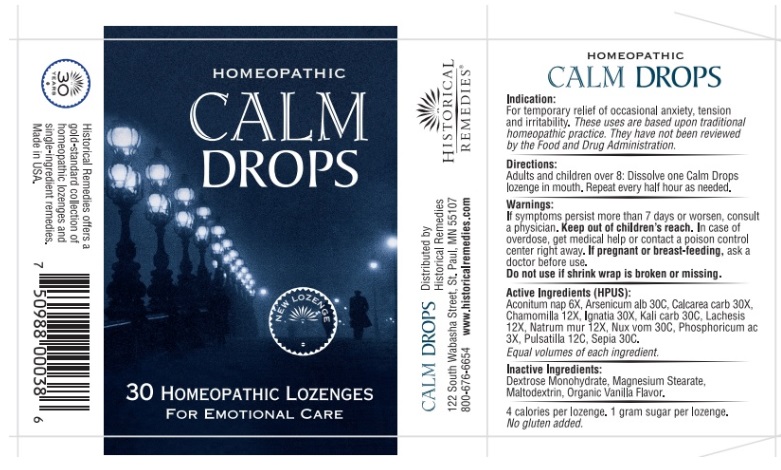 DRUG LABEL: Homeopathic Calm Drops
NDC: 57556-006 | Form: LOZENGE
Manufacturer: HISTORICAL REMEDIES LLP.
Category: homeopathic | Type: HUMAN OTC DRUG LABEL
Date: 20251007

ACTIVE INGREDIENTS: ARSENIC TRIOXIDE 30 [hp_C]/1 1; MATRICARIA CHAMOMILLA 12 [hp_X]/1 1; ARABICA COFFEE BEAN 30 [hp_X]/1 1; POTASSIUM CARBONATE 30 [hp_C]/1 1; STRYCHNOS IGNATII SEED 30 [hp_X]/1 1; LACHESIS MUTA VENOM 12 [hp_X]/1 1; PHOSPHORIC ACID 3 [hp_X]/1 1; PULSATILLA VULGARIS WHOLE 12 [hp_C]/1 1; VALERIAN 30 [hp_C]/1 1; ACONITUM NAPELLUS WHOLE 6 [hp_X]/1 1; SODIUM CHLORIDE 12 [hp_X]/1 1; STRYCHNOS NUX-VOMICA SEED 30 [hp_C]/1 1
INACTIVE INGREDIENTS: DEXTROSE MONOHYDRATE; MAGNESIUM STEARATE; MALTODEXTRIN; ACHLYS TRIPHYLLA WHOLE

CALM DROPS

Indications

For temporary relief of occasional anxiety, tension and irritability. These uses are based upon traditional homeopathic practice. They have not been reviewed by the Food and Drug Administration.

Aconitum nap 6X, Arsenicum alb 30C, Calcarea carb 30X, Chamomilla 12X, Ignatia 30X, Kali carb 30C, Lachesis 12X, Natrum mur 12X, Nux vom 30C, Phosphoricum ac 3X, Pulsatilla 12C, Sepia 30C.

Equal volumes of each ingredient.

Directions

Adults and children over 8: Dissolve one Calm Drops lozenge in mouth. Repeat every half hour as needed.

Warnings

If symptoms persist more than 7 days or worsen, consult a physician. Keep out of children's reach.In case of overdose, get medical help or contact a poison control center right away. If pregnant or breast-feeding,ask a doctor before use. Do not use if shrink wrap is broken or missing.

Active ingredients

Aconitum nap 6X, Arsenicum alb 30C, Calcarea carb 30X, Chamomilla 12X, lgnatia 30X, Kali carb 30C, Lachesis 12X, Natrum mur 12X, Nux vom 30C, Phosphoricum ac 3X, Pulsatilla 12C, Sepia 30C.

Inactive ingredients

Dextrose Monohydrate, Magnesium Stearate, Maltodextrin, Organic Vanilla Flavor.

4 calories per lozenge. 1 gram sugar per lozenge. No gluten added.